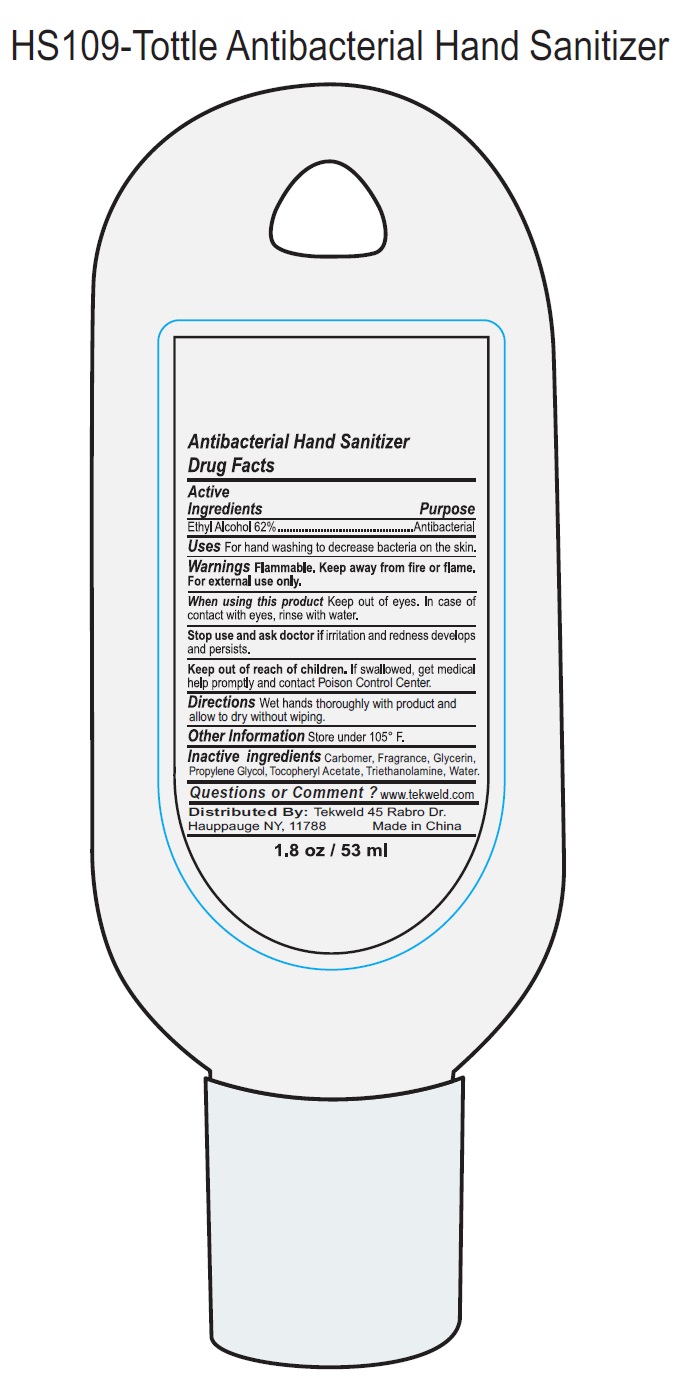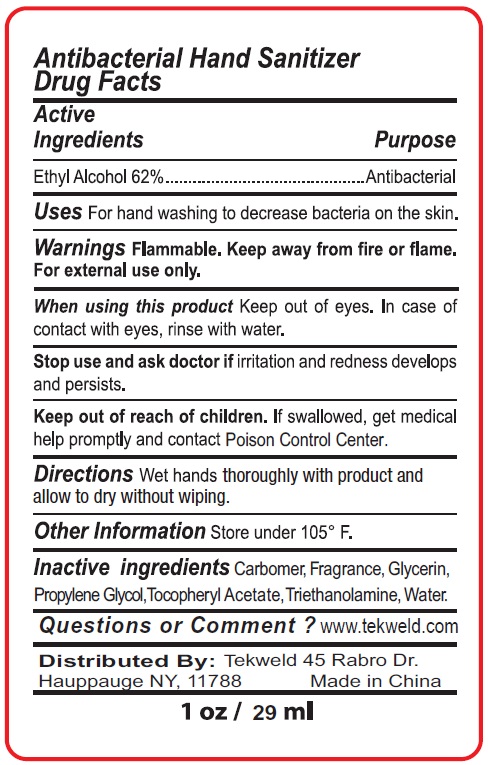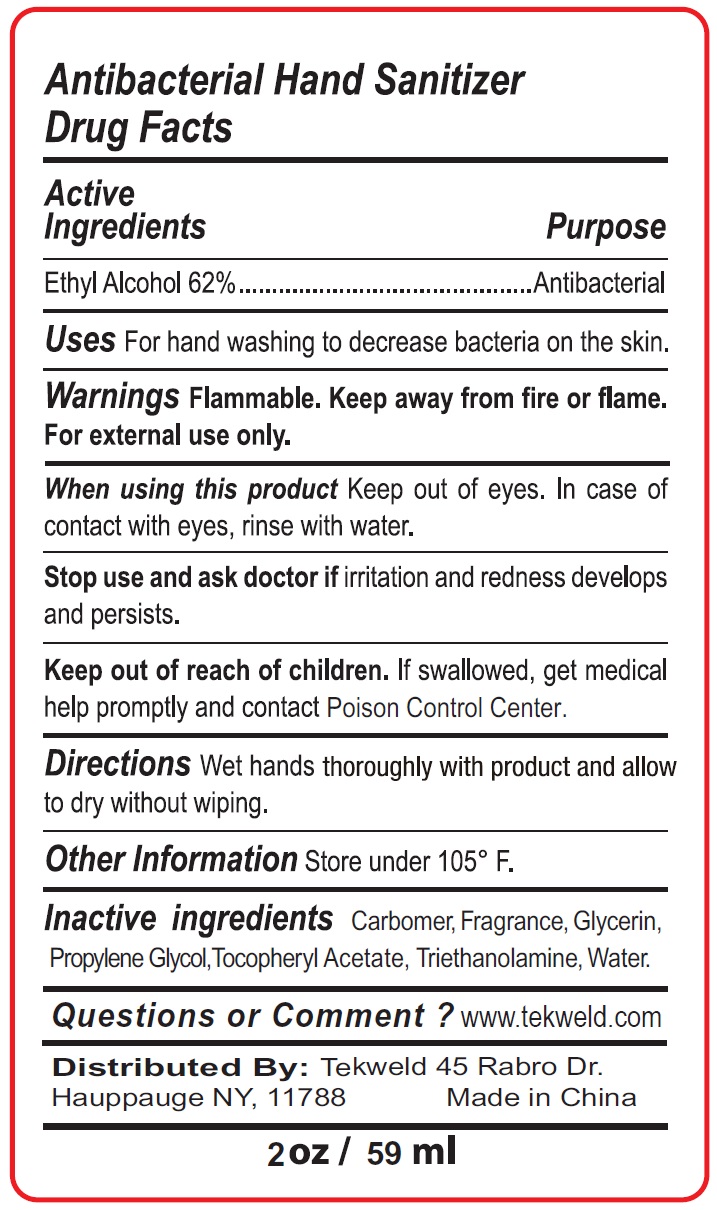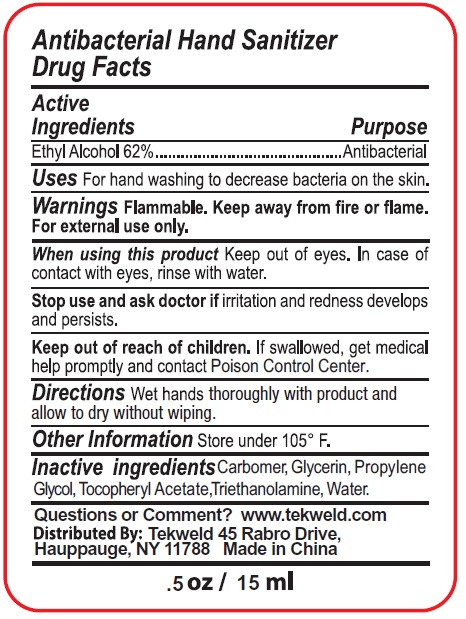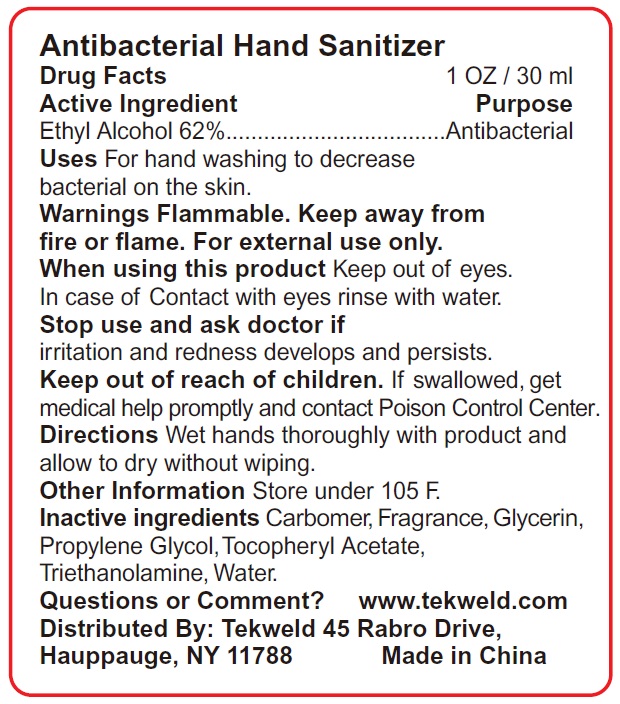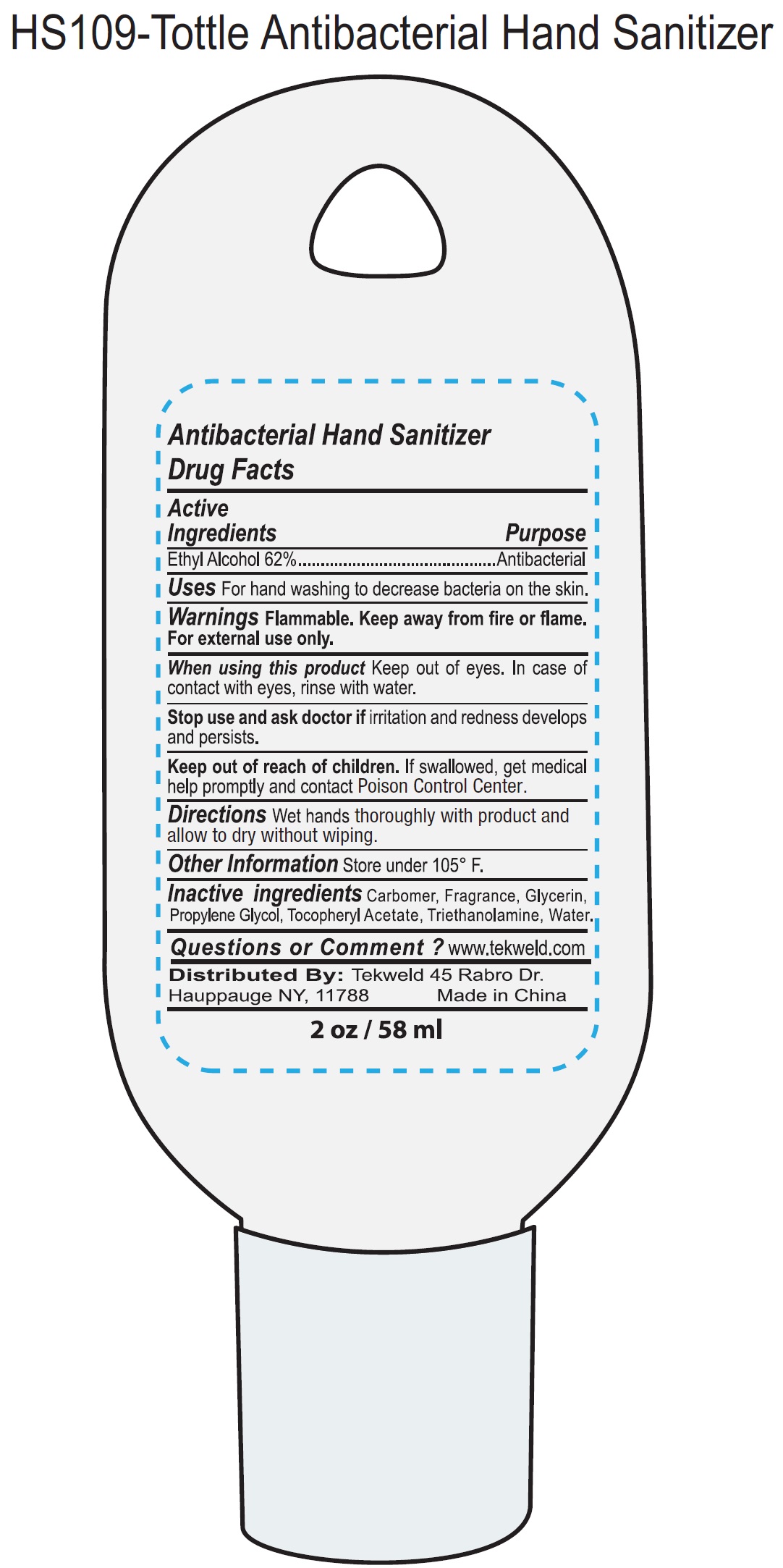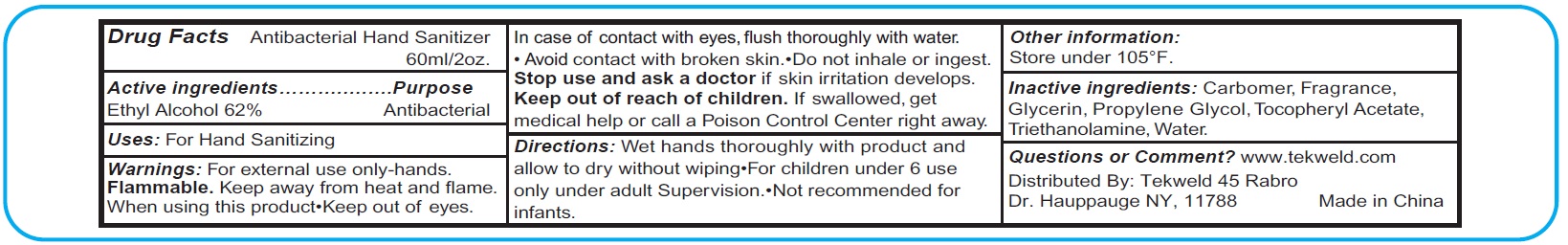 DRUG LABEL: Antibacterial Hand Sanitizer
NDC: 71160-180 | Form: GEL
Manufacturer: TEKWELD SOLUTIONS, INC.
Category: otc | Type: HUMAN OTC DRUG LABEL
Date: 20241203

ACTIVE INGREDIENTS: ALCOHOL 620 mg/1 mL
INACTIVE INGREDIENTS: CARBOXYPOLYMETHYLENE; GLYCERIN; PROPYLENE GLYCOL; .ALPHA.-TOCOPHEROL ACETATE; TROLAMINE; WATER

Antibacterial Hand Sanitizer

Active Ingredients

Ethyl Alcohol 62%

Purpose

Antibacterial

Uses

For hand washing to decrease bacteria on the skin.

Warnings Flammable.

Keep away from fire or flame. For external use only.

When using this product

Keep out of eyes. In case of contact with eyes, rinse with water.

Stop use and ask doctor if

irritation and redness develops and persists.

Keep out of reach of children.

If swallowed, get medical help promptly and contact Poison Control Center.

Directions

Wet hands throughly with product and allow to dry without wiping.

Other Information

Store under 105°F.

Inactive Ingredients

Carbomer,Fragrance,Glycerin,Propylene Glycol, Tocopheryl Acetate,Triethanolamine,Water.

Questions or Comments?

www.tekweld.com